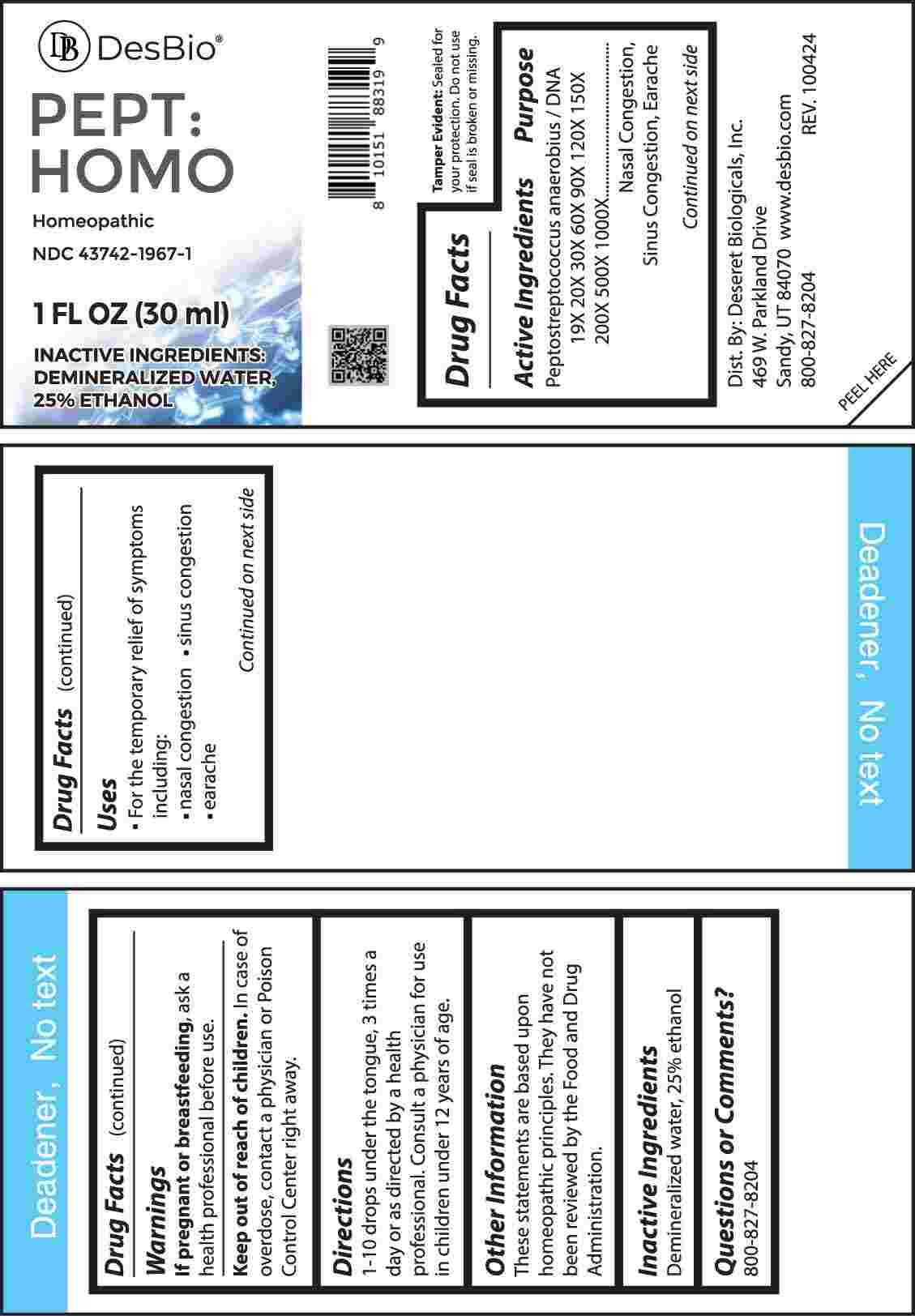 DRUG LABEL: PEPT HOMO
NDC: 43742-1967 | Form: LIQUID
Manufacturer: Deseret Biologicals, Inc.
Category: homeopathic | Type: HUMAN OTC DRUG LABEL
Date: 20250304

ACTIVE INGREDIENTS: PEPTOSTREPTOCOCCUS ANAEROBIUS DNA 19 [hp_X]/1 mL
INACTIVE INGREDIENTS: WATER; ALCOHOL

DRUG FACTS:

ACTIVE INGREDIENTS:

Peptostreptococcus Anaerobius / DNA 19X, 20X, 30X, 60X, 90X, 120X, 150X, 200X, 500X, 1000X.

PURPOSE:

Peptostreptococcus Anaerobius / DNA - Nasal Congestion, Sinus Congestion, Earache

USES:

• For the temporary relief of symptoms including:

• nasal congestion • sinus congestion • earache

These statements are based upon homeopathic principles. They have not been reviewed by the Food and Drug Administration.

WARNINGS:

If pregnant or breastfeeding, ask a health professional before use.

Keep out of reach of children. In case of overdose, contact a physician or poison Control Center right away.

Tamper Evident: Sealed for your protection. Do not use if seal is broken or missing.

KEEP OUT OF REACH OF CHILDREN:

In case of overdose, contact a physician or Poison Control Center right away.

DIRECTIONS:

1-10 drops under the tongue, 3 times a day or as directed by a health professional. Consult a physician for use in children under 12 years of age.

INACTIVE INGREDIENTS:

Demineralized water, 25% ethanol

QUESTIONS:

Dist. By: Deseret Biologicals, Inc.
469 W. Parkland Drive
Sandy, UT 84070

www.desbio.com

800-827-8204

PACKAGE LABEL DISPLAY:

Des Bio

PEPT:HOMO

Homeopathic

NDC 43742-1967-1

1 FL OZ (30 ml)